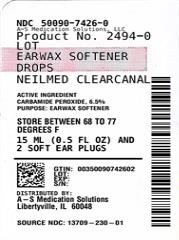 DRUG LABEL:  CLEARCANAL EAR WAX SOFTERNER DROPS
NDC: 50090-7426 | Form: SOLUTION/ DROPS
Manufacturer: A-S Medication Solutions
Category: otc | Type: HUMAN OTC DRUG LABEL
Date: 20241104

ACTIVE INGREDIENTS: CARBAMIDE PEROXIDE 65 mg/1 mL
INACTIVE INGREDIENTS: GLYCERIN; OXYQUINOLINE

CLEARCANAL EAR WAX SOFTERNER DROPS

Drug Facts:

Active ingredient: CARBAMIDE PEROXIDE

Ear Wax Removal Drops Directions

Step 1 Ear Wax Removal Drops Directions:

- FOR USE IN THE EAR ONLY.
- Adults and children over 12 years of age: tilt head sideways and place 5 to 10 drops into ear.
- Tip of applicator should not enter ear canal.
- Keep drops in ear for several minutes by keeping head tilted or placing enclosed ear plugs in ear.
- Use twice daily for upto 4 days if needed or as directed by a doctor.
- Any wax remaining after treatment may be removed by gently flushing the ear with NeilMed ClearCanal rinsing system with special ear rinse adapter.
- Children under 12 years of age: consult a doctor.

STORAGE AND HANDLING

Avoid exposing bottle to excessive heat and direct sunlight. Keep cap on bottle when not in use.

INACTIVE INGREDIENT

Inactive Ingredients: Glycerin, Oxyquinoline, Aloe Barbadensis, Chamomile

PURPOSE

Softens ear wax. Ear wax removal drops

ASK DOCTOR

Children under 12 years of age: consult a doctor.

Keep out of reach of children. If swallowed, get medical help or contact a Poison Control Center right away. If accidental contact with eyes occurs, flush eyes with water and consult a doctor.

Do not use:
* If you have had an allergic reaction to Carbamide Peroxide.
* If you have ear drainage or discharge, ear pain, irritation or rash in the ear, or are dizzy; consult a doctor
* If you have an injury or perforation (hole) of the eardrum or after ear surgery, unless directed by a doctor
* For more than four consecutive days

Stop use ad ask a doctor if excessive ear wax remains after use of this product for four consecutive days

When using this product:
* Avoid contact with the eyes

DESCRIPTION

Ear Wax Removal Complete System

Ear wax is an important part of your body's system for keeping dirt, bacteria and other things from causing hearing problems. When rinsing is necessary, this cleaning system helps to soften, loosen and remove the excessive ear wax.

The system consists of kit with 1 bottle carbamide peroxide solution 15mL and 1 can sterile saline spray 177mL (or 125mL).

DOSAGE AND ADMINISTRATION

Place 5 to 10 drops of 6.5% carbamide peroxide solution into e

Warnings:
Do not use:
If you have had an allergic reaction to carbamide peroxide.
If you have ear drainage or discharge, ear pain, irritation or rash in the ear, or are dizzy; consult a doctor
If you have an injury or perforation (hole) of the eardrum or after ear surgery, unless directed by a doctor
For more than four consecutive days
When using this product:
void contact with the eyes
Stop use ad ask a doctor if excessive ear wax remains after use of this product for four consecutive days.

HOW SUPPLIED

Product: 50090-7426

NDC: 50090-7426-0 15 mL in a BOTTLE, DROPPER / 1 in a BOX